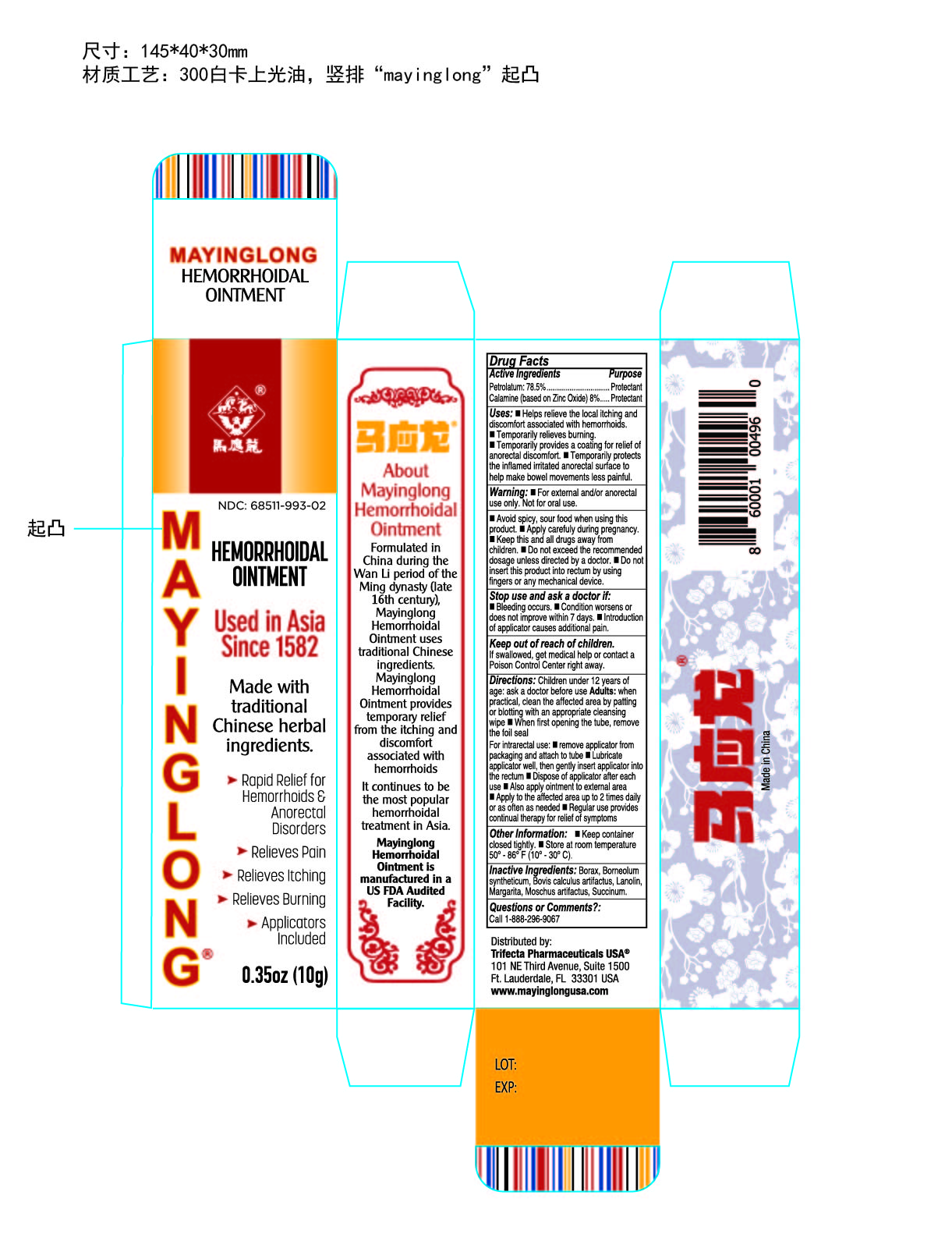 DRUG LABEL: MAYINGLONG HEMORRHOIDS
NDC: 68511-993 | Form: OINTMENT
Manufacturer: Mayinglong Pharmaceutical Group Co Ltd
Category: otc | Type: HUMAN OTC DRUG LABEL
Date: 20190819

ACTIVE INGREDIENTS: ZINC OXIDE 800 mg/10000 mg; PETROLATUM 7850 mg/10000 mg
INACTIVE INGREDIENTS: MUSK KETONE; PEARL (HYRIOPSIS CUMINGII); BORNEOL; SODIUM BORATE; LANOLIN

MAYINGLONG HEMORRHOIDS OINTMENT

Active Ingredients

Zinc Oxide 0.8g Astrigent

Petrolatum 7.85g Protectant

Purpose

Astrigent

Protectant

Protectant

Uses

helps relieve the local itching and discomfort associated with hemorrhoids

temporarily shrinks hemorrhoidal tissue and relieves burning

temporarily provides a coating for relief of anorectal discomforts

temporarily protects the inflamed, irritated anorectal surface to help make bowel movements less painful

Warning

For external and /or intrarectal use only. Not for oral use.

Stop use

bleeding occurs

condition worses or does not improve within 7 days

introduction of applicator into the rectum causes additional pain

Warning

Apply it carfully during pregnancy.

Warning

Keep this and all drugs out of reach of children.

Direction

Apply properly onto anus or apply on affected areas twice a day.

Other information

Store at 20-25 degree Centigrade (68-77 degree Fahrenheit)

Inactive ingredients

Musk Ketone

Pearl (Hyriopsis Cumming II)

Borneol

Sodium Borate